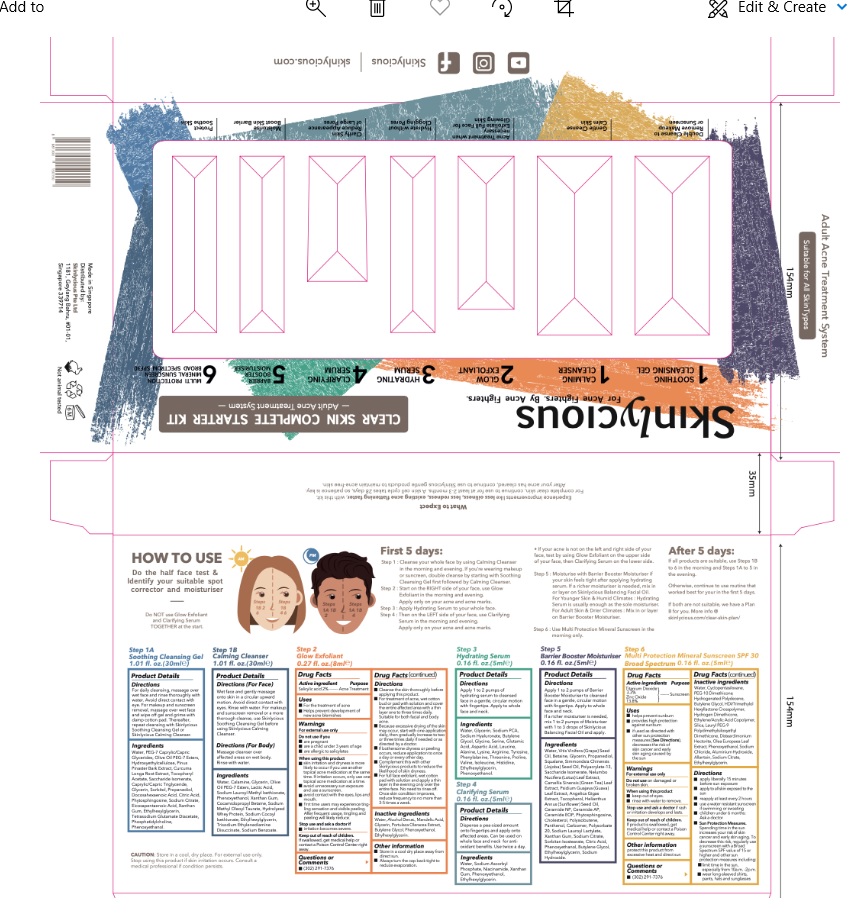 DRUG LABEL: skinlycious Clear skin complete starter kit
NDC: 81574-004 | Form: KIT | Route: TOPICAL
Manufacturer: Skinlycious Pte Ltd
Category: otc | Type: HUMAN OTC DRUG LABEL
Date: 20251003

ACTIVE INGREDIENTS: SALICYLIC ACID 2 g/100 mL; TITANIUM DIOXIDE 3.3 g/100 mL; ZINC OXIDE 13.8 g/100 mL
INACTIVE INGREDIENTS: WATER; ALCOHOL; MANDELIC ACID; GLYCERIN; PURSLANE; BUTYLENE GLYCOL; PHENOXYETHANOL; ETHYLHEXYLGLYCERIN; CYCLOMETHICONE 5; PEG-10 DIMETHICONE (600 CST); HYDROGENATED POLYDECENE TYPE I; BUTYLENE GLYCOL; HEXAMETHYLENE DIISOCYANATE/TRIMETHYLOL HEXYLLACTONE CROSSPOLYMER; HYDROGEN DIMETHICONE (13 CST); ACRYLIC ACID/ETHYLENE COPOLYMER (600 MPA.S); SILICON DIOXIDE; LAURYL PEG-9 POLYDIMETHYLSILOXYETHYL DIMETHICONE; DISTEARDIMONIUM HECTORITE; OLEA EUROPAEA LEAF; PHENOXYETHANOL; SODIUM CHLORIDE; ALUMINUM HYDROXIDE; ALLANTOIN; SODIUM CITRATE; WATER; ETHYLHEXYLGLYCERIN

Active ingredient

Salicylic Acid 2%

Purpose

Acne treatment

Uses

• For the treatment of acne
• Helps prevent development of new acne blemishes

Warnings

For External Use Only
Do not use if
• are pregnant
• are a child under 3 years of age
• are allergic to salicylates

When using this product
• skin irritation and dryness is more likely to occur if you use another topical acne medication at the same time. If irritation occurs, only use one topical acne medication at a time.
• Avoid unnecessary sun exposure and use a sunscreen.
• Avoid contact with the eyes, lips and mouth.
• First time users may experience tingling sensation and visible peeling. After frequent usage, tingling and peeling will likely reduce.

Stop use and ask a doctor if
• Irritation becomes severe

Keep out of reach of children

If swallowed, get medical help or contact a Poison Control Center right away.

Questions or Comments

(302) 291-7376

Direction

• Cleanse the skin thoroughly before applying this product
• For treatment of acne, wet cotton bud or pad with solution and cover the entire affected area with a thin layer one to three times daily. Suitable for both facial and body acne.
• Because excessive drying of the skin may occur, start with one application daily, then gradually increase to two or three times daily if needed or as directed by a doctor.
• If bothersome dryness or peeling occurs, reduce application to once a day or every other day.
• Complement this with other Skinlycious products to reduce the likelihood of skin dryness.
• For full face exfoliant, wet cotton pad with a solution and apply a thin layer in the evening only over the entire face. No need to rinse off. Once skin condition improves, reduce frequency to no more than 3-5 times a week in the evening only.

Inactive Ingredients

Water, Alcohol Denat. Mandelic Acid, Glycerin, Purslane, Butylene Glycol, Phenoxyethanol, Ethylhexylglycerin.

Other information

• Store in a cool dry place away from direct sun.

Active ingredients

Titanium Dioxide 3.3%

Zinc Oxide 13.8%

Purpose

Sunscreen

Uses

• helps prevent sunburn
• provides high protection against sunburn
• if used as directed with other sun protection measures (See Directions), decreases the risk of skin cancer and early skin aging caused by the sun

Warnings

For External Use Only
Do not use on damaged or broken skin.
When using this product
• Keep out of eyes.
• Rinse with water to remove.

Stop use and ask a doctor if rash or irritation develops and lasts.

Keep out of reach of children

If product is swallowed, get medical help or contact a Poison Control Center right away.

Directions

• Apply liberally 15 minutes before sun exposure.
• Apply to all skin exposed to the sun.
• Reapply at least every 2 hours.
• Use a water resistant sunscreen if swimming or sweating.
• Children under 6 months: ask a doctor.
• Sun Protection Measures Spending time in the sun increases your risk of skin cancer and early skin aging. To decrease this risk, regularly use a sunscreen with a Broad Spectrum SPF value of 15 or higher and other sun protection measures including :
- limit time in the sun, especially from 10a.m.-2p.m.
- wear long-sleeved shirts, pants, hats and sunglasses.

Inactive Ingredients

Water, Cyclopentasiloxane, PEG-10 Dimethicone, Hydrogenated Polydecene, Butylene Glycol, HDI/Trimethylol Hexyllactone Crosspolymer, Hydrogen Dimethicone, Ethylene/Acrylic Acid Copolymer, Silica, Lauryl PEG-9 Polydimethylsiloxyethyl Dimethicone, Disteardimonium Hectorite, Olea Europaea Leaf Extract, Phenoxyethanol, Sodium Chloride, Aluminium Hydroxide, Allantoin, Sodium Citrate, Ethylhexylglycerin.

Other information

• protect this product from excessive heat and direct sun